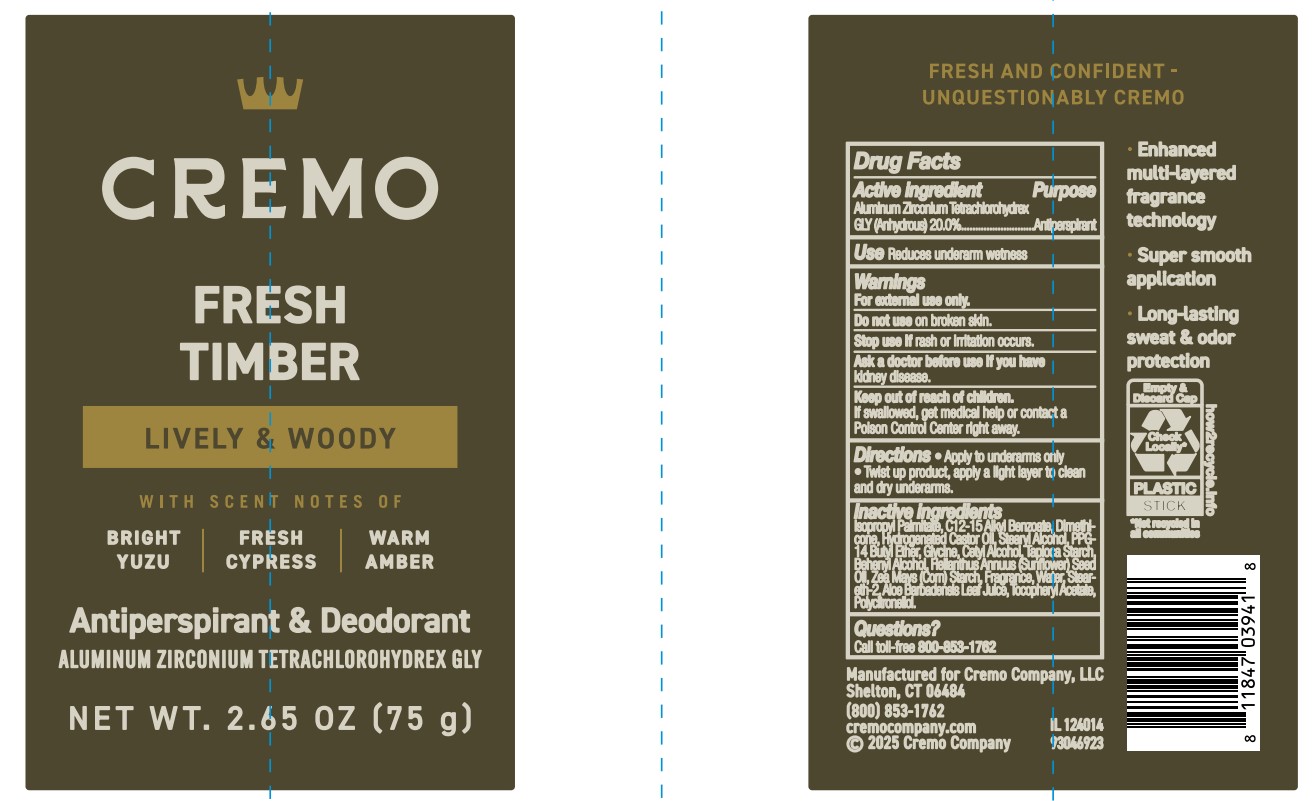 DRUG LABEL: Cremo Company
NDC: 71825-141 | Form: STICK
Manufacturer: Cremo Company
Category: otc | Type: HUMAN OTC DRUG LABEL
Date: 20260125

ACTIVE INGREDIENTS: ALUMINUM ZIRCONIUM TETRACHLOROHYDREX GLY 20 g/100 mL
INACTIVE INGREDIENTS: ISOPROPYL PALMITATE; DIMETHICONE; CETYL ALCOHOL; TAPIOCA STARCH; HELIANTHUS ANNUUS (SUNFLOWER) SEED OIL; ZEA MAYS (CORN) STARCH; WATER; C12-15 ALKYL BENZOATE; STEARYL ALCOHOL; ALOE BARBADENSIS LEAF JUICE; .ALPHA.-TOCOPHEROL ACETATE; PPG-14 BUTYL ETHER; GLYCINE; BEHENYL ALCOHOL; STEARETH-2; HYDROGENATED CASTOR OIL

Active Ingredient

Aluminum Zirconium Tetrachlorohydrex GLY (Anhydrous)

Purpose

Antiperspirant

Uses

Reduces underarm wetness

Warnings

For external use only

Do not use

on broken skin

Stop use if

if skin rash or irritation occurs

Ask a doctor before use if you have

kidney disease

Keep out of reach of children

If swallowed, get medical help or contact a Poison Control Center right away

Directions

• Apply to underarms only. • Twist up product, apply a light layer to clean and dry underarms

Inactive ingredients

Isopropyl Palmitate, C12-15 Alkyl Benzoate, Dimethicone, Hydrogenated Castor Oil, Stearyl Alcohol, PPG-14 Butyl Ether, Glycine, Cetyl Alcohol, Tapioca Starch, Behenyl Alcohol, Helianthus Annuus (Sunflower) Seed Oil, Zea Mays (Corn) Starch, Fragrance, Water, Steareth-2, Aloe Barbadensis Leaf Juice, Tocopheryl Acetate, Polycitronellol

Questions?

Call toll-free 800-853-1762

PACKAGE LABEL

Cremo
FRESH TIMBER
LIVELY & WOODY
WITH SCENT NOTES OF
BRIGHT YUZU| FRESH CYPRESS | WARM AMBER
Antiperspirant & Deodorant
ALUMINUM ZIRCONIUM TETRACHLOROHYDREX GLY
NET WT. 2.65 OZ (75 g)